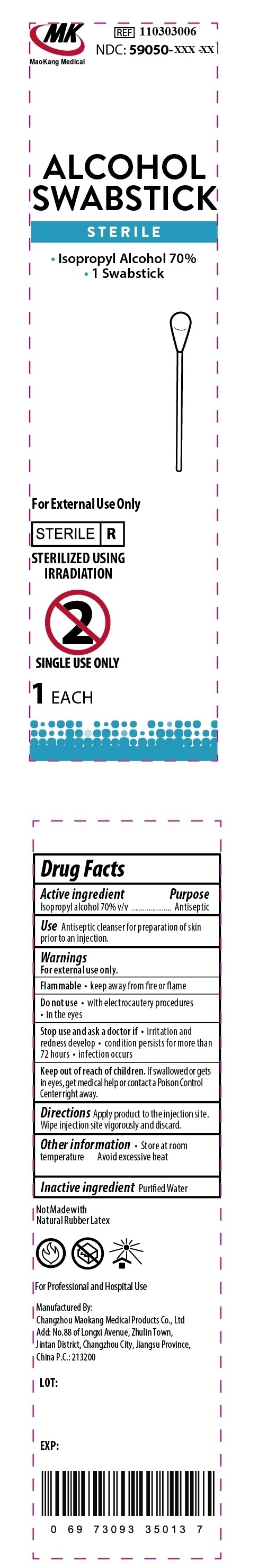 DRUG LABEL: Alcohol Swabstick Isopropyl Alcohol 70
NDC: 59050-266 | Form: LIQUID
Manufacturer: Changzhou Maokang Medical Products Co., Ltd
Category: otc | Type: HUMAN OTC DRUG LABEL
Date: 20231109

ACTIVE INGREDIENTS: ISOPROPYL ALCOHOL 70 mL/100 mL
INACTIVE INGREDIENTS: WATER

Alcohol Swabstick Isopropyl Alcohol 70%

Active ingredient

Isopropyl alcohol 70% v/v

Purpose

Antiseptic

Use

Antiseptic cleanser for preparation of skin prior to an injection.

Warnings

For external use only.

• keep away from fire or flame Flammable

Do not use

• with electrocauteryl procedures

• in the eyes

Stop use and ask a doctor if

• irritation and redness develop • condition persists for more than 72 hours • infection occurs

Keep out of reach of children.

If swallowed or gets in eyes, get medical help or contact a Poison Control Center right away

Directions

Apply product to the injection site. Wipe injection site vigorously and discard.

Other information

• Store at room temperature Avoid excessive heat

Inactive ingredient

Purified Water